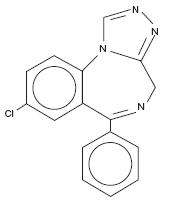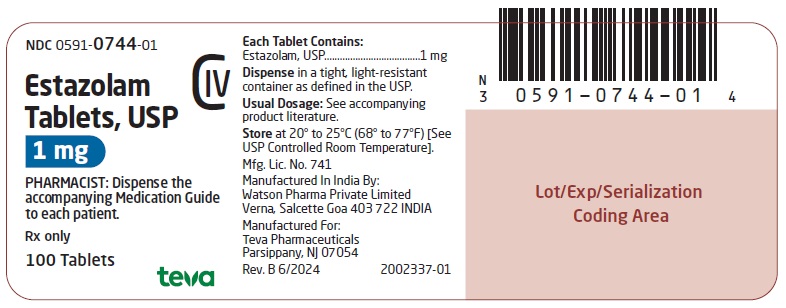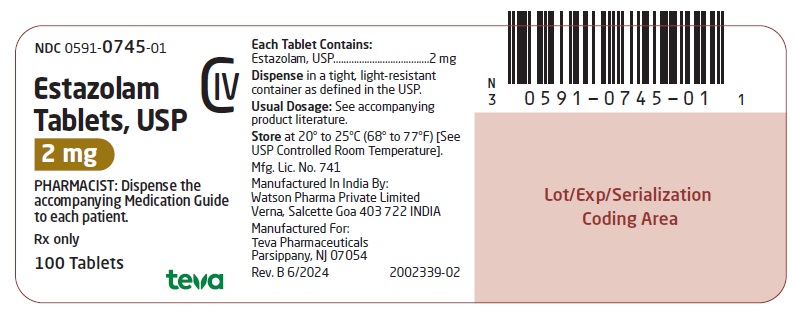 DRUG LABEL: Estazolam
NDC: 0591-0744 | Form: TABLET
Manufacturer: Actavis Pharma, Inc.
Category: prescription | Type: HUMAN PRESCRIPTION DRUG LABEL
Date: 20240630
DEA Schedule: CIV

ACTIVE INGREDIENTS: ESTAZOLAM 1 mg/1 1
INACTIVE INGREDIENTS: DOCUSATE SODIUM; LACTOSE MONOHYDRATE; MAGNESIUM STEARATE; MICROCRYSTALLINE CELLULOSE; SODIUM BENZOATE; SODIUM STARCH GLYCOLATE TYPE A POTATO; STEARIC ACID

Estazolam Tablets, USP C-IV
Rx only

BOXED WARNING

WARNING: RISKS FROM CONCOMITANT USE WITH OPIOIDS; ABUSE, MISUSE, AND ADDICTION; and DEPENDENCE AND WITHDRAWAL REACTIONS

- Concomitant use of benzodiazepines and opioids may result in profound sedation, respiratory depression, coma, and death (see WARNINGS).
- Reserve concomitant prescribing of these drugs in patients for whom alternative treatment options are inadequate. Limit dosages and durations to the minimum required. Follow patients for signs and symptoms of respiratory depression and sedation (see WARNINGS and PRECAUTIONS).
- The use of benzodiazepines, including estazolam, exposes users to risks of abuse, misuse, and addiction, which can lead to overdose or death. Abuse and misuse of benzodiazepines commonly involve concomitant use of other medications, alcohol, and/or illicit substances, which is associated with an increased frequency of serious adverse outcomes. Before prescribing estazolam and throughout treatment, assess each patient’s risk for abuse, misuse, and addiction (see WARNINGS).
- The continued use of benzodiazepines, including estazolam, may lead to clinically significant physical dependence. The risks of dependence and withdrawal increase with longer treatment duration and higher daily dose. Abrupt discontinuation or rapid dosage reduction of estazolam after continued use may precipitate acute withdrawal reactions, which can be life-threatening. To reduce the risk of withdrawal reactions, use a gradual taper to discontinue estazolam or reduce the dosage (see DOSAGE AND ADMINISTRATION and WARNINGS).

DESCRIPTION

Estazolam, USP, a triazolobenzodiazepine derivative, is an oral hypnotic agent. Estazolam occurs as a fine, white, odorless powder that is soluble in alcohol and practically insoluble in water. The chemical name for estazolam is 8-chloro-6-phenyl-4H-s-triazolo[4,3-α][1,4]benzodiazepine. The structural formula is represented as follows:

C16H11ClN4 M. W. 294.75

Each tablet, for oral administration, contains either 1 mg or 2 mg of estazolam, USP. In addition, each tablet contains the following inactive ingredients: docusate sodium, lactose monohydrate, magnesium stearate, microcrystalline cellulose, sodium benzoate, sodium starch glycolate and stearic acid. The 2 mg tablets also contain FD&C Red #40 Aluminum Lake.

CLINICAL PHARMACOLOGY

Pharmacokinetics

Absorption

Estazolam tablets have been found to be equivalent in absorption to an orally administered solution of estazolam. In healthy subjects who received up to three times the recommended dose of estazolam, peak estazolam plasma concentrations occurred within two hours after dosing (range 0.5 to 6 hours) and were proportional to the administered dose, suggesting linear pharmacokinetics over the dosage range tested.

Distribution

Independent of concentration, estazolam in plasma is 93% protein bound.

Metabolism

Estazolam is extensively metabolized. Only two metabolites (1-oxo-estazolam and 4-hydroxy-estazolam) were detected in human plasma up to 18 hours.

The pharmacologic activity of estazolam is primarily from the parent drug. The elimination of the parent drug takes place via hepatic metabolism of estazolam to hydroxylated and other metabolites that are eliminated largely in the urine both free and conjugated. In humans, greater than 70% of a single dose of estazolam was recovered in the urine as metabolites. Less than 5% of a 2 mg dose of estazolam was excreted unchanged in the urine, with only 4% of the dose appearing in the feces. The principal urinary excretion product is an unidentified metabolite, presumed to be a metabolic product of 4-hydroxy-estazolam, accounting for at least 27% of the administered dose. 4-hydroxy-estazolam is the major metabolite in plasma, with concentrations approaching 12% of those of the parent eight hours after administration. Urinary 4-hydroxy-estazolam and 1-oxo-estazolam account for 11.9% and 4.4% of the dose respectively. In vitro studies with human liver microsomes indicate that the biotransformation of estazolam to the major circulating metabolite 4-hydroxy-estazolam is mediated by cytochrome P450 3A (CYP3A). While 4-hydroxy-estazolam and the lesser metabolite, 1-oxo-estazolam, have some pharmacologic activity, their low potencies and low concentrations preclude any significant contribution to the hypnotic effect of estazolam.

Elimination

The range of estimates for the mean elimination half-life of estazolam varied from 10 to 24 hours. Radiolabel mass balance studies indicate that the main route of excretion is via the kidneys. After 5 days, 87% of the administered radioactivity was excreted in human urine. Less than 4% of the dose was excreted unchanged. Eleven metabolites were found in urine. Four metabolites were identified as 1-oxo-estazolam, 4’-hydroxy-estazolam, 4-hydroxy-estazolam, and benzophenone, as free metabolites and glucuronides. The predominant metabolite in urine (17% of the administered dose) has not been identified, but is likely to be a metabolite of 4-hydroxy-estazolam.

Special Populations

In a small study (N=8) using various doses in older subjects (59 to 68 years), peak estazolam concentrations were found to be similar to those observed in younger subjects with a mean elimination half-life of 18.4 hours (range 13.5 to 34.6 hours). The influence of hepatic or renal impairment on the pharmacokinetics of estazolam has not been studied.

Pediatrics

The pharmacokinetics of estazolam have not been studied in pediatric patients.

Race

The influence of race on the pharmacokinetics of estazolam has not been studied.

Gender

The gender-effect on the pharmacokinetics of estazolam has not been investigated.

Cigarette Smoking

The clearance of benzodiazepines is accelerated in smokers compared to nonsmokers, and there is evidence that this occurs with estazolam. This decrease in half-life, presumably due to enzyme induction by smoking, is consistent with other drugs with similar hepatic clearance characteristics. In all subjects and at all doses, the mean elimination half-life appeared to be independent of the dose.

Drug-Drug Interaction

The metabolism of estazolam to the major circulating metabolite 4-hydroxy-estazolam is catalyzed by CYP3A. While no in vivo drug-drug interaction studies were conducted between estazolam and inhibitors/inducers of CYP3A, compounds that are potent CYP3A inhibitors (such as ketoconazole, itraconazole, nefazodone, fluvoxamine, and erythromycin) would be expected to increase plasma estazolam concentrations and CYP3A inducers (such as carbamazepine, phenytoin, rifampin and barbiturates) would be expected to decrease estazolam concentrations.

Drug Interaction with Fluoxetine

A multiple-dose study was conducted to assess the effect of fluoxetine 20 mg BID on the pharmacokinetics of estazolam 2 mg QHS after seven days. The pharmacokinetics of estazolam (Cmax and AUC) were not affected during multiple-dose fluoxetine, suggesting no clinically significant pharmacokinetic interaction.

The Ability of Estazolam to Induce or Inhibit Human Enzyme Systems

The results from in vitro human liver microsomal studies suggest that at therapeutic concentrations, estazolam has no significant inhibitory effect on the major human cytochrome P450 enzyme activities (i.e., CYP1A2, CYP2A6, CYP2C9, CYP2C19, CYP2D6, CYP2E1, and CYP3A). The ability of estazolam to induce human hepatic enzyme systems has not been determined.

Pharmacodynamics

Postulated relationship between elimination rate of benzodiazepine hypnotics and their profile of common untoward effects: The type and duration of hypnotic effects and the profile of unwanted effects during administration of benzodiazepine drugs may be influenced by the biologic half-life of administered drug and any active metabolites formed. If half-lives are long, drug or metabolites may accumulate during periods of nightly administration and may be associated with impairments of cognitive and/or motor performance during waking hours; the possibility of interaction with other psychoactive drugs or alcohol will be increased. In contrast, if half-lives are short, drug and metabolites will be cleared before the next dose is ingested, and carry-over effects related to excessive sedation or CNS depression should be minimal or absent. However, during nightly use for an extended period, pharmacodynamic tolerance or adaptation to some effects of benzodiazepine hypnotics may develop. If the drug has a short elimination half-life, it is possible that a relative deficiency of the drug or its active metabolites (i.e., in relationship to the receptor site) may occur at some point in the interval between each night’s use. This sequence of events may account for two clinical findings reported to occur after several weeks of max nightly use of rapidly eliminated benzodiazepine hypnotics, namely, increased wakefulness during the last third of the night and increased daytime anxiety in selected patients.

CLINICAL STUDIES

Controlled Trials Supporting Efficacy
In three 7 night, double-blind, parallel-group trials comparing estazolam 1 mg and/or 2 mg with placebo in adult outpatients with chronic insomnia, estazolam 2 mg was consistently superior to placebo in subjective measures of sleep induction (latency) and sleep maintenance (duration, number of awakenings, depth and quality of sleep); estazolam 1 mg was similarly superior to placebo on all measures of sleep maintenance, however, it significantly improved sleep induction in only one of two studies. In a similarly designed trial comparing estazolam 0.5 mg and 1 mg with placebo in geriatric outpatients with chronic insomnia, only the 1 mg estazolam dose was consistently superior to placebo in sleep induction (latency) and in only one measure of sleep maintenance (i.e., duration of sleep).

In a single-night, double-blind, parallel-group trial comparing estazolam 2 mg and placebo in patients admitted for elective surgery and requiring sleep medications, estazolam was superior to placebo in subjective measures of sleep induction and maintenance.

In a 12 week, double-blind, parallel-group trial including a comparison of estazolam 2 mg and placebo in adult outpatients with chronic insomnia, estazolam was superior to placebo in subjective measures of sleep induction (latency) and maintenance (duration, number of awakenings, total wake time during sleep) at week 2, but produced consistent improvement over 12 weeks only for sleep duration and total wake time during sleep. Following withdrawal at week 12, rebound insomnia was seen at the first withdrawal week, but there was no difference between drug and placebo by the second withdrawal week in all parameters except latency, for which normalization did not occur until the fourth withdrawal week.

Adult outpatients with chronic insomnia were evaluated in a sleep laboratory trial comparing four doses of estazolam (0.25, 0.5, 1 and 2 mg) and placebo, each administered for 2 nights in a crossover design. The higher estazolam doses were superior to placebo in most EEG measures of sleep induction and maintenance, especially at the 2 mg dose, but only for sleep duration in subjective measures of sleep.

INDICATIONS AND USAGE

Estazolam tablets, USP are indicated for the short-term management of insomnia characterized by difficulty in falling asleep, frequent nocturnal awakenings, and/or early morning awakenings. Both outpatient studies and a sleep laboratory study have shown that estazolam administered at bedtime improved sleep induction and sleep maintenance (see CLINICAL PHARMACOLOGY).

Because insomnia is often transient and intermittent, the prolonged administration of estazolam is generally neither necessary nor recommended. Since insomnia may be a symptom of several other disorders, the possibility that the complaint may be related to a condition for which there is a more specific treatment should be considered.

There is evidence to support the ability of estazolam to enhance the duration and quality of sleep for intervals up to 12 weeks (see CLINICAL PHARMACOLOGY).

CONTRAINDICATIONS

Estazolam is contraindicated with ketoconazole and itraconazole, since these medications significantly impair oxidative metabolism mediated by CYP3A (see WARNINGS and PRECAUTIONS, Drug Interactions).

WARNINGS

Risks from Concomitant Use with Opioids
Concomitant use of benzodiazepines, including estazolam, and opioids may result in profound sedation, respiratory depression, coma, and death. Because of these risks, reserve concomitant prescribing of these drugs in patients for whom alternative treatment options are inadequate.

Observational studies have demonstrated that concomitant use of opioid analgesics and benzodiazepines increases the risk of drug-related mortality compared to use of opioids alone. If a decision is made to prescribe estazolam concomitantly with opioids, prescribe the lowest effective dosages and minimum durations of concomitant use, and follow patients closely for signs and symptoms of respiratory depression and sedation. In patients already receiving an opioid analgesic, prescribe a lower initial dose of estazolam than indicated in the absence of an opioid and titrate based on clinical response. If an opioid is initiated in a patient already taking estazolam, prescribe a lower initial dose of the opioid and titrate based upon clinical response.

Advise both patients and caregivers about the risks of respiratory depression and sedation when estazolam is used with opioids. Advise patients not to drive or operate heavy machinery until the effects of concomitant use with the opioid have been determined (see PRECAUTIONS, Drug Interactions).

Abuse, Misuse, and Addiction
The use of benzodiazepines, including estazolam, exposes users to the risks of abuse, misuse, and addiction, which can lead to overdose or death. Abuse and misuse of benzodiazepines often (but not always) involve the use of doses greater than the maximum recommended dosage and commonly involve concomitant use of other medications, alcohol, and/or illicit substances, which is associated with an increased frequency of serious adverse outcomes, including respiratory depression, overdose, or death (see DRUG ABUSE AND DEPENDENCE, Abuse).

Before prescribing estazolam and throughout treatment, assess each patient’s risk for abuse, misuse, and addiction (e.g., using a standardized screening tool). Use of estazolam, particularly in patients at elevated risk, necessitates counseling about the risks and proper use of estazolam along with monitoring for signs and symptoms of abuse, misuse, and addiction. Prescribe the lowest effective dosage; avoid or minimize concomitant use of CNS depressants and other substances associated with abuse, misuse, and addiction (e.g., opioid analgesics, stimulants); and advise patients on the proper disposal of unused drug. If a substance use disorder is suspected, evaluate the patient and institute (or refer them for) early treatment, as appropriate.

Dependence and Withdrawal Reactions
To reduce the risk of withdrawal reactions, use a gradual taper to discontinue estazolam or reduce the dosage (a patient-specific plan should be used to taper the dose) (see DOSAGE AND ADMINISTRATION, Discontinuation or Dosage Reduction of Estazolam).

Patients at an increased risk of withdrawal adverse reactions after benzodiazepine discontinuation or rapid dosage reduction include those who take higher dosages, and those who have had longer durations of use.

Acute Withdrawal Reactions
The continued use of benzodiazepines, including estazolam, may lead to clinically significant physical dependence. Abrupt discontinuation or rapid dosage reduction of estazolam after continued use, or administration of flumazenil (a benzodiazepine antagonist) may precipitate acute withdrawal reactions, which can be life-threatening (e.g., seizures) (see DRUG ABUSE AND DEPENDENCE, Dependence).

Protracted Withdrawal Syndrome
In some cases, benzodiazepine users have developed a protracted withdrawal syndrome with withdrawal symptoms lasting weeks to more than 12 months (see DRUG ABUSE AND DEPENDENCE, Dependence).

Because sleep disturbances may be the presenting manifestation of a physical and/or psychiatric disorder, symptomatic treatment of insomnia should be initiated only after a careful evaluation of the patient. The failure of insomnia to remit after 7 to 10 days of treatment may indicate the presence of a primary psychiatric and/or medical illness that should be evaluated. Worsening of insomnia or the emergence of new thinking or behavior abnormalities may be the consequence of an unrecognized psychiatric or physical disorder. Such findings have emerged during the course of treatment with sedative-hypnotic drugs. Because some of the important adverse effects of sedative-hypnotics appear to be dose-related (see PRECAUTIONS and DOSAGE AND ADMINISTRATION), it is important to use the smallest possible effective dose, especially in the elderly.

Complex behaviors such as “sleep-driving” (i.e., driving while not fully awake after ingestion of a sedative-hypnotic, with amnesia for the event) have been reported. These events can occur in sedative-hypnotic-naïve as well as in sedative-hypnotic-experienced persons. Although behaviors such as sleep driving may occur with sedative-hypnotics alone at therapeutic doses, the use of alcohol and other CNS depressants with sedative-hypnotics appears to increase the risk of such behaviors, as does the use of sedative-hypnotics at doses exceeding the maximum recommended dose. Due to the risk to the patient and the community, discontinuation of sedative-hypnotics should be strongly considered for patients who report a “sleep-driving” episode.

Other complex behaviors (e.g., preparing and eating food, making phone calls, or having sex) have been reported in patients who are not fully awake after taking a sedative-hypnotic. As with sleep-driving, patients usually do not remember these events.

Because sedative-hypnotics can cause drowsiness and a decreased level of consciousness, patients, particularly the elderly, are at higher risk of falls.

Severe Anaphylactic and Anaphylactoid Reactions
Rare cases of angioedema involving the tongue, glottis or larynx have been reported in patients after taking the first or subsequent doses of sedative-hypnotics, including estazolam. Some patients have had additional symptoms such as dyspnea, throat closing, or nausea and vomiting that suggest anaphylaxis. Some patients have required medical therapy in the emergency department. If angioedema involves the tongue, glottis or larynx, airway obstruction may occur and be fatal. Patients who develop angioedema after treatment with estazolam should not be rechallenged with the drug.

Estazolam, like other benzodiazepines, has CNS depressant effects. For this reason, patients should be cautioned against engaging in hazardous occupations requiring complete mental alertness, such as operating machinery or driving a motor vehicle, after ingesting the drug, including potential impairment of the performance of such activities that may occur the day following ingestion of estazolam. Patients should also be cautioned about possible combined effects with alcohol and other CNS depressant drugs.

As with all benzodiazepines, amnesia, paradoxical reactions (e.g., excitement, agitation, etc.), and other adverse behavioral effects may occur unpredictably.

Estazolam Interaction with Drugs That Inhibit Metabolism via Cytochrome P450 3A (CYP3A)

The metabolism of estazolam to the major circulating metabolite 4-hydroxy-estazolam and the metabolism of other triazolobenzodiazepines is catalyzed by CYP3A. Consequently, estazolam should be avoided in patients receiving ketoconazole and itraconazole, which are very potent inhibitors of CYP3A (see CONTRAINDICATIONS). With drugs inhibiting CYP3A to a lesser, but still significant degree, estazolam should be used only with caution and consideration of appropriate dosage reduction. The following are examples of drugs known to inhibit the metabolism of other related benzodiazepines, presumably through inhibition of CYP3A: nefazodone, fluvoxamine, cimetidine, diltiazem, isoniazid, and some macrolide antibiotics.

While no in vivo drug-drug interaction studies were conducted between estazolam and inducers of CYP3A, compounds that are potent CYP3A inducers (such as carbamazepine, phenytoin, rifampin, and barbiturates) would be expected to decrease estazolam concentrations.

Neonatal Sedation and Withdrawal Syndrome
Use of estazolam late in pregnancy can result in sedation (respiratory depression, lethargy, hypotonia) and/or withdrawal symptoms (hyperreflexia, irritability, restlessness, tremors, inconsolable crying, and feeding difficulties) in the neonate (see PRECAUTIONS: Pregnancy). Monitor neonates exposed to estazolam during pregnancy or labor for signs of sedation and monitor neonates exposed to estazolam during pregnancy for signs of withdrawal; manage these neonates accordingly.

PRECAUTIONS

General

Impaired motor and/or cognitive performance attributable to the accumulation of benzodiazepines and their active metabolites following several days of repeated use at their recommended doses is a concern in certain vulnerable patients (e.g., those especially sensitive to the effects of benzodiazepines or those with a reduced capacity to metabolize and eliminate them) (see DOSAGE AND ADMINISTRATION).

Elderly or debilitated patients and those with impaired renal or hepatic function should be cautioned about these risks and advised to monitor themselves for signs of excessive sedation or impaired conditions.

Estazolam appears to cause dose-related respiratory depression that is ordinarily not clinically relevant at recommended doses in patients with normal respiratory function. However, patients with compromised respiratory function may be at risk and should be monitored appropriately. As a class, benzodiazepines have the capacity to depress respiratory drive; there are insufficient data available, however, to characterize their relative potency in depressing respiratory drive at clinically recommended doses.

As with other benzodiazepines, estazolam should be administered with caution to patients exhibiting signs or symptoms of depression. Suicidal tendencies may be present in such patients and protective measures may be required. Intentional overdosage is more common in this group of patients; therefore, the least amount of drug that is feasible should be prescribed for the patient at any one time.

Information for Patients

Advise the patient to read the FDA-approved patient labeling (Medication Guide).

Risks from Concomitant Use with Opioids

Advise both patients and caregivers about the risks of potentially fatal respiratory depression and sedation when estazolam is used with opioids and not to use such drugs concomitantly unless supervised by a health care provider. Advise patients not to drive or operate heavy machinery until the effects of concomitant use with the opioid have been determined (see WARNINGS: Risks from Concomitant Use with Opioids and PRECAUTIONS, Drug Interactions).

Abuse, Misuse, and Addiction

Inform patients that the use of estazolam, even at recommended dosages, exposes users to risks of abuse, misuse, and addiction, which can lead to overdose and death, especially when used in combination with other medications (e.g., opioid analgesics), alcohol, and/or illicit substances. Inform patients about the signs and symptoms of benzodiazepine abuse, misuse, and addiction; to seek medical help if they develop these signs and/or symptoms; and on the proper disposal of unused drug (see WARNINGS, Abuse, Misuse, and Addiction and DRUG ABUSE AND DEPENDENCE).

Withdrawal Reactions

Inform patients that the continued use of estazolam may lead to clinically significant physical dependence and that abrupt discontinuation or rapid dosage reduction of estazolam may precipitate acute withdrawal reactions, which can be life-threatening. Inform patients that in some cases, patients taking benzodiazepines have developed a protracted withdrawal syndrome with withdrawal symptoms lasting weeks to more than 12 months. Instruct patients that discontinuation or dosage reduction of estazolam may require a slow taper (see WARNINGS, Dependence and Withdrawal Reactions and DRUG ABUSE AND DEPENDENCE).

“Sleep-Driving” and Other Complex Behaviors

There have been reports of people getting out of bed after taking a sedative-hypnotic and driving their cars while not fully awake, often with no memory of the event. If a patient experiences such an episode, it should be reported to his or her doctor immediately, since “sleep-driving” can be dangerous. This behavior is more likely to occur when sedative-hypnotics are taken with alcohol or other central nervous system depressants (see WARNINGS). Other complex behaviors (e.g., preparing and eating food, making phone calls, or having sex) have been reported in patients who are not fully awake after taking a sedative-hypnotic. As with sleep-driving, patients usually do not remember these events.

Inform your physician about any alcohol consumption and medicine you are taking now, including drugs you may buy without a prescription. Alcohol should not be used during treatment with hypnotics.

Inform your physician if you are planning to become pregnant, if you are pregnant, or if you become pregnant while you are taking this medicine.

You should not take this medicine if you are nursing, as the drug may be excreted in breast milk.

Until you experience the way this medicine affects you, do not drive a car, operate potentially dangerous machinery, or engage in hazardous occupations requiring complete mental alertness after taking this medicine.

Advise patients that increased drowsiness and decreased consciousness may increase the risk of falls in some patients.

Pregnancy

Advise pregnant females that use of estazolam late in pregnancy can result in sedation (respiratory depression, lethargy, hypotonia) and/or withdrawal symptoms (hyperreflexia, irritability, restlessness, tremors, inconsolable crying, and feeding difficulties) in newborns (see WARNINGS: Neonatal Sedation and Withdrawal Syndrome and PRECAUTIONS: Pregnancy). Instruct patients to inform their healthcare provider if they are pregnant.

Advise patients that there is a pregnancy exposure registry that monitors pregnancy outcomes in women exposed to estazolam during pregnancy (see PRECAUTIONS, Pregnancy).

Nursing

Advise patients that breastfeeding is not recommended during treatment with estazolam (see PRECAUTIONS: Nursing Mothers).

Laboratory Tests

Laboratory tests are not ordinarily required in otherwise healthy patients. When treatment with estazolam is protracted, periodic blood counts, urinalyses, and blood chemistry analyses are advisable.

Drug Interactions

The concomitant use of benzodiazepines and opioids increases the risk of respiratory depression because of actions at different receptor sites in the CNS that control respiration. Benzodiazepines interact at GABAA sites and opioids interact primarily at mu receptors. When benzodiazepines and opioids are combined, the potential for benzodiazepines to significantly worsen opioid-related respiratory depression exists.

Limit dosage and duration of concomitant use of benzodiazepines and opioids, and monitor patients closely for respiratory depression and sedation.

If estazolam is given concomitantly with other drugs acting on the central nervous system, careful consideration should be given to the pharmacology of all agents. The action of the benzodiazepines may be potentiated by anticonvulsants, antihistamines, alcohol, barbiturates, monoamine oxidase inhibitors, narcotics, phenothiazines, psychotropic medications, or other drugs that produce CNS depression. Smokers have an increased clearance of benzodiazepines as compared to nonsmokers; this was seen in studies with estazolam (see CLINICAL PHARMACOLOGY).

While no in vivo drug-drug interaction studies were conducted between estazolam and inducers of CYP3A, compounds that are potent CYP3A inducers (such as carbamazepine, phenytoin, rifampin, and barbiturates) would be expected to decrease estazolam concentrations.

Estazolam Interaction with Drugs that Inhibit Metabolism via Cytochrome P450 3A (CYP3A)

The metabolism of estazolam to the major circulating metabolite 4-hydroxy-estazolam and the metabolism of other triazolobenzodiazepines is catalyzed by CYP3A. Consequently, estazolam should be avoided in patients receiving ketoconazole and itraconazole, which are very potent inhibitors of CYP3A (see CONTRAINDICATIONS). With drugs inhibiting CYP3A to a lesser, but still significant degree, estazolam should be used only with caution and consideration of appropriate dosage reduction. The following are examples of drugs known to inhibit the metabolism of other related benzodiazepines, presumably through inhibition of CYP3A: nefazodone, fluvoxamine, cimetidine, diltiazem, isoniazid, and some macrolide antibiotics.

Drug Interaction with Fluoxetine

A multiple-dose study was conducted to assess the effect of fluoxetine 20 mg BID on the pharmacokinetics of estazolam 2 mg QHS after seven days. The pharmacokinetics of estazolam (Cmax and AUC) were not affected during multiple-dose fluoxetine, suggesting no clinically significant pharmacokinetic interaction.

Estazolam Interaction with Other Drugs That are Metabolized by Cytochrome P450 (CYP)

At clinically relevant concentrations, in vitro studies indicate that estazolam (0.6μM) was not inhibitory towards the major cytochrome P450 isoforms CYP1A2, CYP2A6, CYP2C9, CYP2C19, CYP2D6, CYP2E1, and CYP3A. Therefore, based on these in vitro data, estazolam is very unlikely to inhibit the biotransformation of other drugs metabolized by these CYP isoforms.

Carcinogenesis, Mutagenesis, Impairment of Fertility

Two-year carcinogenicity studies were conducted in mice and rats at dietary doses of 0.8, 3, and 10 mg/kg/day and 0.5, 2, and 10 mg/kg/day, respectively. Evidence of tumorigenicity was not observed in either study. Incidence of hyperplastic liver nodules increased in female mice given the mid- and high-dose levels. The significance of such nodules in mice is not known at this time.

In vitro and in vivo mutagenicity tests including the Ames test, DNA repair in B. subtilis, in vivo cytogenetics in mice and rats, and the dominant lethal test in mice did not show a mutagenic potential for estazolam.

Fertility in male and female rats was not affected by doses up to 30 times the usual recommended human dose.

Pregnancy

Pregnancy Exposure Registry

There is a pregnancy registry that monitors pregnancy outcomes in women exposed to psychiatric medications, including estazolam, during pregnancy. Healthcare providers are encouraged to register patients by calling the National Pregnancy Registry for Psychiatric Medications at 1-866-961-2388 or visiting online at https://womensmentalhealth.org/pregnancyregistry/.

Risk Summary

Neonates born to mothers using benzodiazepines late in pregnancy have been reported to experience symptoms of sedation and/or neonatal withdrawal (see WARNINGS: Neonatal Sedation and Withdrawal Syndrome and PRECAUTIONS: Clinical Considerations). Available data from published observational studies of pregnant women exposed to benzodiazepines do not report a clear association with benzodiazepines and major birth defects (see Data).

The estimated background risk of major birth defects and miscarriage for the indicated population is unknown. All pregnancies have a background risk of birth defect, loss, or other adverse outcomes. In the U.S. general population, the estimated risk of major birth defects and of miscarriage in clinically recognized pregnancies is 2% to 4% and 15% to 20%, respectively.

Clinical Considerations

Fetal/Neonatal Adverse Reactions

Benzodiazepines cross the placenta and may produce respiratory depression, hypotonia and sedation in neonates. Monitor neonates exposed to estazolam during pregnancy and labor for signs of sedation, respiratory depression, hypotonia, and feeding problems Monitor neonates exposed to estazolam during pregnancy for signs of withdrawal. Manage these neonates accordingly (see WARNINGS: Neonatal Sedation and Withdrawal Syndrome).

Data

Human Data

Published data from observational studies on the use of benzodiazepines during pregnancy do not report a clear association with benzodiazepines and major birth defects. Although early studies reported an increased risk of congenital malformations with diazepam and chlordiazepoxide, there was no consistent pattern noted. In addition, the majority of more recent case-control and cohort studies of benzodiazepine use during pregnancy, which were adjusted for confounding exposures to alcohol, tobacco and other medications, have not confirmed these findings.

Nursing Mothers

There are no data on the presence of estazolam in human milk. Estazolam is present in animal milk. When a drug is present in animal milk, it is likely that the drug will be present in human milk. There are reports of sedation, poor feeding and poor weight gain in infants exposed to benzodiazepines through breast milk. The effects of estazolam on milk production are unknown. Because of estazolam’s long half-life, the potential for estazolam to accumulate in breast milk, and the potential for serious adverse reactions, including sedation and withdrawal symptoms in infants, advise patients that breastfeeding is not recommended during treatment with estazolam.

Pediatric Use

Safety and effectiveness in pediatric patients below the age of 18 have not been established.

Geriatric Use

Approximately 18% of individuals participating in the premarketing clinical trials of estazolam were 60 years of age or older. Overall, the adverse event profile did not differ substantively from that observed in younger individuals. Care should be exercised when prescribing benzodiazepines to small or debilitated elderly patients (see DOSAGE AND ADMINISTRATION).

ADVERSE REACTIONS

Commonly Observed

The most commonly observed adverse events associated with the use of estazolam, not seen at an equivalent incidence among placebo-treated patients were somnolence, hypokinesia, dizziness, and abnormal coordination.

Associated with Discontinuation of Treatment

Approximately 3% of 1277 patients who received estazolam in U.S. premarketing clinical trials discontinued treatment because of an adverse clinical event. The only event commonly associated with discontinuation, accounting for 1.3% of the total, was somnolence.

Incidence in Controlled Clinical Trials

The table below enumerates adverse events that occurred at an incidence of 1% or greater among patients with insomnia who received estazolam in 7-night, placebo-controlled trials. Events reported by investigators were classified into standard dictionary (COSTART) terms to establish event frequencies. Event frequencies reported were not corrected for the occurrence of these events at baseline. The frequencies were obtained from data pooled across six studies: estazolam, N = 685; placebo, N = 433. The prescriber should be aware that these figures cannot be used to predict the incidence of side effects in the course of usual medical practice in which patient characteristics and other factors differ from those that prevailed in these six clinical trials. Similarly, the cited frequencies cannot be compared with figures obtained from other clinical investigators involving related drug products and uses, since each group of drug trials was conducted under a different set of conditions. However, the cited figures provide the physician with a basis of estimating the relative contribution of drug and nondrug factors to the incidence of side effects in the population studied.

INCIDENCE OF ADVERSE EXPERIENCES IN PLACEBO-CONTROLLED CLINICAL TRIALS
(Percentage of Patients Reporting)
 | Estazolam | Placebo
Body System/Adverse Event* | (N=685) | (N=433)
Body as a Whole
Headache | 16 | 27
Asthenia | 11 | 8
Malaise | 5 | 5
Lower extremity pain | 3 | 2
Back pain | 2 | 2
Body pain | 2 | 2
Abdominal pain | 1 | 2
Chest pain | 1 | 1
Digestive System
Nausea | 4 | 5
Dyspepsia | 2 | 2
Musculoskeletal System
Stiffness | 1 | --
Nervous System
Somnolence | 42 | 27
Hypokinesia | 8 | 4
Nervousness | 8 | 11
Dizziness | 7 | 3
Coordination abnormal | 4 | 1
Hangover | 3 | 2
Confusion | 2 | --
Depression | 2 | 3
Dream abnormal | 2 | 2
Thinking abnormal | 2 | 1
Respiratory System
Cold symptoms | 3 | 5
Pharyngitis | 1 | 2
Skin and Appendages
Pruritus | 1 | --
* Events reported by at least 1% of estazolam patients.

Other Adverse Events

During clinical trials, some of which were not placebo-controlled, estazolam was administered to approximately 1300 patients. Untoward events associated with this exposure were recorded by clinical investigators using terminology of their own choosing. To provide a meaningful estimate of the proportion of individuals experiencing adverse events, similar types of untoward events must be grouped into a smaller number of standardized event categories. In the tabulations that follow, a standard COSTART dictionary terminology has been used to classify reported adverse events. The frequencies presented, therefore, represent the proportion of the 1277 individuals exposed to estazolam who experienced an event of the type cited on at least one occasion while receiving estazolam. All reported events are included except those already listed in the previous table, those COSTART terms too general to be informative, and those events where a drug cause was remote. Events are further classified within body system categories and enumerated in order of decreasing frequency using the following definitions: frequent adverse events are defined as those occurring on one or more occasions in at least 1/100 patients; infrequent adverse events are those occurring in 1/100 to 1/1000 patients; rare events are those occurring in less than 1/1000 patients. It is important to emphasize that, although the events reported did occur during treatment with estazolam, they were not necessarily caused by it.

Body as a Whole - Infrequent: allergic reaction, chills, fever, neck pain, upper extremity pain; Rare: edema, jaw pain, swollen breast.

Cardiovascular System - Infrequent: flushing, palpitation; Rare: arrhythmia, syncope.

Digestive System - Frequent: constipation, dry mouth; Infrequent: decreased appetite, flatulence, gastritis, increased appetite, vomiting; Rare: enterocolitis, melena, ulceration of the mouth.

Endocrine System - Rare: thyroid nodule.

Hematologic and Lymphatic System - Rare: leukopenia, purpura, swollen lymph nodes.

Metabolic/Nutritional Disorders - Infrequent: thirst; Rare: increased SGOT, weight gain, weight loss.

Musculoskeletal System - Infrequent: arthritis, muscle spasm, myalgia; Rare: arthralgia.

Nervous System - Frequent: anxiety; Infrequent: agitation, amnesia, apathy, emotional lability, euphoria, hostility, paresthesia, seizure, sleep disorder, stupor, twitch; Rare: ataxia, circumoral paresthesia, decreased libido, decreased reflexes, hallucinations, neuritis, nystagmus, tremor. Minor changes in EEG patterns, usually low-voltage fast activity, have been observed in patients during estazolam therapy or withdrawal and are of no known clinical significance.

Respiratory System - Infrequent: asthma, cough, dyspnea, rhinitis, sinusitis; Rare: epistaxis, hyperventilation, laryngitis.

Skin and Appendages - Infrequent: rash, sweating, urticaria; Rare: acne, dry skin.

Special Senses - Infrequent: abnormal vision, ear pain, eye irritation, eye pain, eye swelling, perverse taste, photophobia, tinnitus; Rare: decreased hearing, diplopia, scotomata.

Urogenital System - Infrequent: frequent urination, menstrual cramps, urinary hesitancy, urinary urgency, vaginal discharge/itching; Rare: hematuria, nocturia, oliguria, penile discharge, urinary incontinence.

Postintroduction Reports - Voluntary reports of non-U.S. postmarketing experience with estazolam have included rare occurrences of photosensitivity, Stevens-Johnson syndrome, and agranulocytosis. Because of the uncontrolled nature of these spontaneous reports, a causal relationship to estazolam treatment has not been determined.

To report SUSPECTED ADVERSE REACTIONS, contact Teva at 1-888-838-2872 or FDA at 1-800-FDA-1088 or www.fda.gov/medwatch.

DRUG ABUSE AND DEPENDENCE

Controlled Substance

Estazolam is a controlled substance in Schedule IV.

Abuse

Estazolam is a benzodiazepine and a CNS depressant with a potential for abuse and addiction. Abuse is the intentional, non-therapeutic use of a drug, even once, for its desirable psychological or physiological effects. Misuse is the intentional use, for therapeutic purposes, of a drug by an individual in a way other than prescribed by a health care provider or for whom it was not prescribed. Drug addiction is a cluster of behavioral, cognitive, and physiological phenomena that may include a strong desire to take the drug, difficulties in controlling drug use (e.g., continuing drug use despite harmful consequences, giving a higher priority to drug use than other activities and obligations), and possible tolerance or physical dependence. Even taking benzodiazepines as prescribed may put patients at risk for abuse and misuse of their medication. Abuse and misuse may lead to addiction.

Abuse and misuse of benzodiazepines often (but not always) involve the use of doses greater than the maximum recommended dosage and commonly involve concomitant use of other medications, alcohol, and/or illicit substances, which is associated with an increased frequency of serious adverse outcomes, including respiratory depression, overdose, or death. Benzodiazepines are often sought by individuals who abuse drugs and other substances, and by individuals with addictive disorders (see WARNINGS, Abuse, Misuse, and Addiction).

The following adverse reactions have occurred with benzodiazepine abuse and/or misuse: abdominal pain, amnesia, anorexia, anxiety, aggression, ataxia, blurred vision, confusion, depression, disinhibition, disorientation, dizziness, euphoria, impaired concentration and memory, indigestion, irritability, muscle pain, slurred speech, tremors, and vertigo.

The following severe adverse reactions have occurred with benzodiazepine abuse and/or misuse: delirium, paranoia, suicidal ideation and behavior, seizures, coma, breathing difficulty, and death. Death is more often associated with polysubstance use (especially benzodiazepines with other CNS depressants such as opioids and alcohol).

Dependence

Physical Dependence

Estazolam may produce physical dependence from continued therapy. Physical dependence is a state that develops as a result of physiological adaptation in response to repeated drug use, manifested by withdrawal signs and symptoms after abrupt discontinuation or a significant dose reduction of a drug. Abrupt discontinuation or rapid dosage reduction of benzodiazepines or administration of flumazenil, a benzodiazepine antagonist, may precipitate acute withdrawal reactions, including seizures, which can be life-threatening. Patients at an increased risk of withdrawal adverse reactions after benzodiazepine discontinuation or rapid dosage reduction include those who take higher dosages (i.e., higher and/or more frequent doses) and those who have had longer durations of use (see WARNINGS, Dependence and Withdrawal Reactions).

To reduce the risk of withdrawal reactions, use a gradual taper to discontinue estazolam or reduce the dosage (see DOSAGE AND ADMINISTRATION, Discontinuation or Dosage Reduction of estazolam and WARNINGS, Dependence and Withdrawal Reactions).

Acute Withdrawal Signs and Symptoms

Acute withdrawal signs and symptoms associated with benzodiazepines have included abnormal involuntary movements, anxiety, blurred vision, depersonalization, depression, derealization, dizziness, fatigue, gastrointestinal adverse reactions (e.g., nausea, vomiting, diarrhea, weight loss, decreased appetite), headache, hyperacusis, hypertension, irritability, insomnia, memory impairment, muscle pain and stiffness, panic attacks, photophobia, restlessness, tachycardia, and tremor. More severe acute withdrawal signs and symptoms, including life-threatening reactions, have included catatonia, convulsions, delirium tremens, depression, hallucinations, mania, psychosis, seizures, and suicidality.

Protracted Withdrawal Syndrome

Protracted withdrawal syndrome associated with benzodiazepines is characterized by anxiety, cognitive impairment, depression, insomnia, formication, motor symptoms (e.g., weakness, tremor, muscle twitches), paresthesia, and tinnitus that persists beyond 4 to 6 weeks after initial benzodiazepine withdrawal. Protracted withdrawal symptoms may last weeks to more than 12 months. As a result, there may be difficulty in differentiating withdrawal symptoms from potential re-emergence or continuation of symptoms for which the benzodiazepine was being used.

Tolerance

Tolerance to estazolam may develop from continued therapy. Tolerance is a physiological state characterized by a reduced response to a drug after repeated administration (i.e., a higher dose of a drug is required to produce the same effect that was once obtained at a lower dose). Tolerance to the therapeutic effect of estazolam may develop; however, little tolerance develops to the amnestic reactions and other cognitive impairments caused by benzodiazepines.

OVERDOSAGE

Overdosage of benzodiazepines is characterized by central nervous system depression ranging from drowsiness to coma. In mild to moderate cases, symptoms can include drowsiness, confusion, dysarthria, lethargy, hypnotic state, diminished reflexes, ataxia, and hypotonia. Rarely, paradoxical or disinhibitory reactions (including agitation, irritability, impulsivity, violent behavior, confusion, restlessness, excitement, and talkativeness) may occur. In severe overdosage cases, patients may develop respiratory depression and coma. Overdosage of benzodiazepines in combination with other CNS depressants (including alcohol and opioids) may be fatal (see WARNINGS: Dependence and Withdrawal Reactions). Markedly abnormal (lowered or elevated) blood pressure, heart rate, or respiratory rate raise the concern that additional drugs and/or alcohol are involved in the overdosage.

In managing benzodiazepine overdosage, employ general supportive measures, including intravenous fluids and airway management. Flumazenil, a specific benzodiazepine receptor antagonist, is indicated for the complete or partial reversal of the sedative effects of benzodiazepines in the management of benzodiazepine overdosage, can lead to withdrawal and adverse reactions, including seizures, particularly in the context of mixed overdosage with drugs that increase seizure risk (e.g., tricyclic and tetracyclic antidepressants) and in patients with long-term benzodiazepine use and physical dependency. The risk of withdrawal seizures with flumazenil use may be increased in patients with epilepsy. Flumazenil is contraindicated in patients who have received a benzodiazepine for control of a potentially life-threatening condition (e.g., status epilepticus). If the decision is made to use flumazenil, it should be used as an adjunct to, not as a substitute for, supportive management of benzodiazepine overdosage. See the flumazenil injection Prescribing Information.

Consider contacting a poison center (1-800-222-1222), poisoncontrol.org, or a medical toxicologist for additional overdosage management recommendations.

DOSAGE AND ADMINISTRATION

The recommended initial dose for adults is 1 mg at bedtime; however, some patients may need a 2 mg dose. In healthy elderly patients, 1 mg is also the appropriate starting dose, but increases should be initiated with particular care. In small or debilitated older patients, a starting dose of 0.5 mg, while only marginally effective in the overall elderly population, should be considered.

Discontinuation or Dosage Reduction of Estazolam

To reduce the risk of withdrawal reactions, use a gradual taper to discontinue estazolam or reduce the dosage. If a patient develops withdrawal reactions, consider pausing the taper or increasing the dosage to the previous tapered dosage level. Subsequently decrease the dosage more slowly (see WARNINGS, Dependence and Withdrawal Reactions and DRUG ABUSE AND DEPENDENCE, Dependence).

HOW SUPPLIED

Estazolam tablets USP, 1 mg are white, scored, diamond-shaped tablets, debossed with 744 above the score and 1 below the score on one side, and WATSON on the other side, supplied in bottles of 100 (NDC 0591-0744-01).

Estazolam tablets USP, 2 mg are dark pink, scored, diamond-shaped tablets, debossed with 745 above the score and 2 below the score on one side, and WATSON on the other side, supplied in bottles of 100 (NDC 0591-0745-01).

Store at 20° to 25°C (68° to 77°F) [See USP Controlled Room Temperature].

Dispense in a tight, light-resistant container as defined in the USP, with a child-resistant closure (as required).

Manufactured In India By:
Watson Pharma Private Limited
Verna, Salcette Goa 403 722 INDIA

Manufactured For:
Teva Pharmaceuticals
Parsippany, NJ 07054

Rev. G 6/2024

MEDICATION GUIDE

Estazolam (es taz'oh lam)
Tablets, USP C-IV

What is the most important information I should know about estazolam?

- Estazolam is a benzodiazepine medicine. Taking benzodiazepines with opioid medicines, alcohol, or other central nervous system depressants (CNS) (including street drugs) can cause severe drowsiness, breathing problems (respiratory depression), coma and death. Get emergency help right away if any of the following happens:

- shallow or slowed breathing
- breathing stops (which may lead to the heart stopping)
- excessive sleepiness (sedation)

Do not drive or operate heavy machinery until you know how taking estazolam with opioids affects you.

- Risk of abuse, misuse, and addiction. There is a risk of abuse, misuse, and addiction with benzodiazepines, including estazolam, which can lead to overdose and serious side effects including coma and death.

- Serious side effects including coma and death have happened in people who have abused or misused benzodiazepines, including estazolam. These serious side effects may also include delirium, paranoia, suicidal thoughts or actions, seizures, and difficulty breathing. Call your healthcare provider or go to the nearest hospital emergency room right away if you get any of these serious side effects.
- You can develop an addiction even if you take estazolam exactly as prescribed by your healthcare provider.
- Take estazolam exactly as your healthcare provider prescribed.
- Do not share your estazolam with other people.
- Keep estazolam in a safe place and away from children.

- Physical dependence and withdrawal reactions. Estazolam can cause physical dependence and withdrawal reactions, especially if you continue to take estazolam for several days to several weeks.

- Do not suddenly stop taking estazolam. Stopping estazolam suddenly can cause serious and life-threatening side effects, including unusual movements, responses, or expressions, seizures, sudden and severe mental or nervous system changes, depression, seeing or hearing things that others do not see or hear, an extreme increase in activity or talking, losing touch with reality, and suicidal thoughts or actions. Call your healthcare provider or go to the nearest hospital emergency room right away if you get any of these symptoms.
- Some people who suddenly stop benzodiazepines have symptoms that can last for several weeks to more than 12 months, including, anxiety, trouble remembering, learning, or concentrating, depression, problems sleeping, feeling like insects are crawling under your skin, weakness, shaking, muscle twitching, burning or prickling feeling in your hands, arms, legs or feet, and ringing in your ears.
- Physical dependence is not the same as drug addiction. Your healthcare provider can tell you more about the differences between physical dependence and drug addiction.
- Do not take more estazolam than prescribed or take estazolam for longer than prescribed.

- After taking estazolam, you may get up out of bed while not being fully awake and do an activity that you do not know you are doing. The next morning, you may not remember that you did anything during the night. You have a higher chance for doing these activities if you drink alcohol or take other medicines that make you sleepy with estazolam. Reported activities include:

- driving a car (“sleep-driving”)
- making and eating food
- talking on the phone
- having sex
- sleep-walking

Call your healthcare provider right away if you find out that you have done any of the above activities after taking estazolam.

- Do not take estazolam unless you are able to stay in bed a full night (7 to 8 hours) before you must be active again.

What is estazolam?

- Estazolam is a prescription medicine used short-term to treat certain types of insomnia including difficulty falling asleep, waking up often during the night, or waking up early in the morning.
- Estazolam is a federal controlled substance (C-IV) because it contains estazolam that can be abused or lead to dependence. Keep estazolam in a safe place to prevent misuse and abuse. Selling or giving away estazolam may harm others, and is against the law. Tell your healthcare provider if you have ever abused or been dependent on alcohol, prescription medicines or street drugs.
- It is not known if estazolam is safe and effective in children.
- It is not known if estazolam is safe and effective when used to treat insomnia for longer than 12 weeks.

Do not take estazolam if you:

- are allergic to estazolam, other benzodiazepines, or any of the ingredients in estazolam. See the end of this Medication Guide for a complete list of ingredients in estazolam.
- take antifungal medicines called ketoconazole and itraconazole.

Before you take estazolam, tell your healthcare provider about all of your medical conditions, including if you:

- have a history of depression, mental illness, or suicidal thoughts
- have a history of drug or alcohol abuse or addiction
- have kidney or liver problems
- have lung disease or breathing problems
- are pregnant or plan to become pregnant.

- Taking estazolam late in pregnancy may cause your baby to have symptoms of sedation (breathing problems, sluggishness, low muscle tone), and/or withdrawal symptoms (jitteriness, irritability, restlessness, shaking, excessive crying, feeding problems).
- Tell your healthcare provider right away if you become pregnant or think you are pregnant during treatment with estazolam tablets.
- There is a pregnancy registry for women who take estazolam tablets during pregnancy. The purpose of the registry is to collect information about the health of you and your baby. If you become pregnant during treatment with estazolam tablets, talk to your healthcare provider about registering with the National Pregnancy Registry for Psychiatric Medications. You can register by calling 1-866-961-2388 or visiting https://womensmentalhealth.org/pregnancyregistry/.

- are breastfeeding, or plan to breastfeed.

- Talk to your healthcare provider about the best way to feed your baby if you take estazolam.
- Breastfeeding is not recommended during treatment with estazolam tablets.

Tell your healthcare provider about all of the medicines you take, including prescription and over-the-counter medicines, vitamins, and herbal supplements.

Taking estazolam with certain other medicines can cause side effects or affect how well estazolam or the other medicines work. Do not start or stop other medicines without talking to your healthcare provider.

Do not take estazolam with other medicines that can make you sleepy unless your healthcare provider tells you to.

How should I take estazolam?

- See “What is the most important information I should know about estazolam?”
- Take estazolam exactly as your healthcare provider tells you to take it.
- Take estazolam right before you get into bed. Or you can take estazolam after you have been in bed and have trouble falling asleep.
- Do not take estazolam with or right after a meal.
- Do not take estazolam unless you are able to get a full night’s sleep before you must be active again.
- If you take too much estazolam, get emergency treatment right away.

What are the possible side effects of estazolam?

Estazolam may cause serious side effects, including:

- See “What is the most important information I should know about estazolam?”
- Other conditions. Call your healthcare provider if your insomnia worsens or is not better within 7 to 10 days. This may mean that there is another condition causing your sleep problem.
- Severe allergic reactions. Symptoms include swelling of the tongue or throat, and trouble breathing. Get emergency medical help right away if you have these symptoms after taking estazolam.
- Abnormal thoughts and behavior. Symptoms include more outgoing or aggressive behavior than normal, confusion, agitation, hallucinations, worsening of depression, and suicidal thoughts.
- Estazolam can make you sleepy or dizzy and can slow your thinking and motor skills.

- Do not drive, operate heavy machinery, or do other dangerous activities until you know how estazolam affects you.
- Do not drink alcohol or take other medicines that may make you sleepy or dizzy while taking estazolam without first talking to your healthcare provider. When taken with alcohol or medicines that cause sleepiness or dizziness, estazolam may make your sleepiness or dizziness much worse.

The most common side effects of estazolam include:

- drowsiness

- headache

- fatigue

- dizziness

- dry mouth

- upset stomach

You may still feel drowsy the next day after taking ESTAZOLAM. Do not drive or do other dangerous activities after taking ESTAZOLAM until you feel fully awake.

These are not all the possible side effects of estazolam. Call your doctor for medical advice about side effects. You may report side effects to FDA at 1-800-FDA-1088.

How should I store estazolam?

- Store estazolam tablets in a tightly closed child resistant container at room temperature between 68° to 77°F (20° to 25°C).
- Keep estazolam and all medicines out of the reach of children.

General information about the safe and effective use of estazolam.

Medicines are sometimes prescribed for purposes other than those listed in a Medication Guide. Do not use estazolam for a condition for which it was not prescribed. Do not give estazolam to other people, even if they have the same symptoms that you have. It may harm them. You can ask your healthcare provider or pharmacist for information about estazolam that is written for healthcare professionals.

What are the ingredients in estazolam?

Active Ingredient: estazolam

Inactive Ingredients: docusate sodium, lactose monohydrate, magnesium stearate, microcrystalline cellulose, sodium benzoate, sodium starch glycolate and stearic acid. The 2 mg tablets also contain FD&C Red #40 Aluminum Lake.

Manufactured In India By: Watson Pharma Private Limited, Verna, Salcette Goa 403 722 INDIA
Manufactured For: Teva Pharmaceuticals, Parsippany, NJ 07054

If you would like more information, call Teva at 1-888-838-2872.

This Medication Guide has been approved by the U.S. Food and Drug Administration. Rev. E 6/2024

PRINCIPAL DISPLAY PANEL

NDC 0591-0744-01
CIV
Estazolam Tablets, USP
1mg
PHARMACIST: Dispense the accompanying Medication Guide to each patient.
Rx only
100 Tablets

PRINCIPAL DISPLAY PANEL

NDC 0591-0745-01
CIV
Estazolam Tablets, USP
2 mg
PHARMACIST: Dispense the accompanying Medication Guide to each patient.
Rx only
100 Tablets